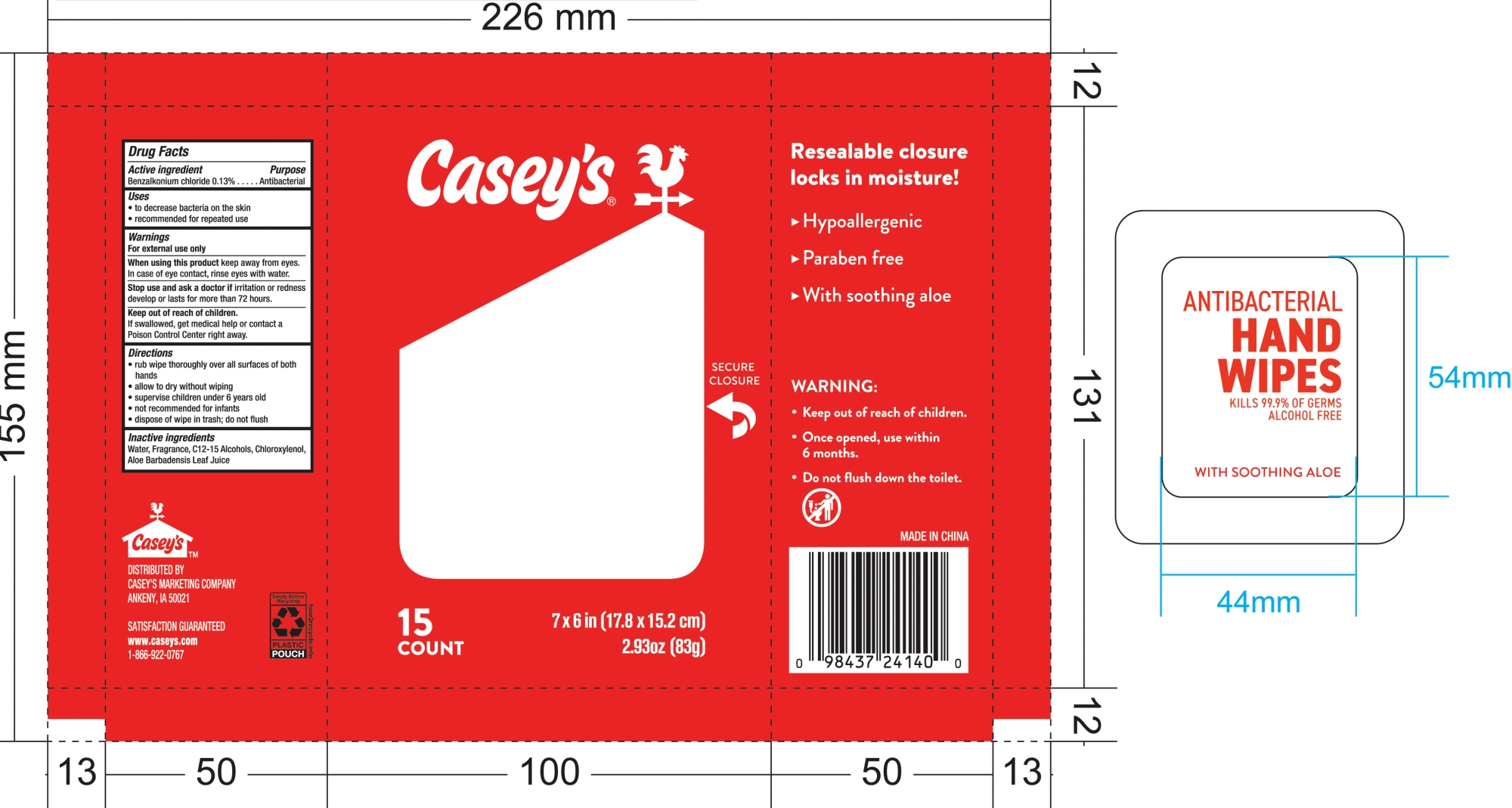 DRUG LABEL: CASEYS ANTIBACTERIAL HAND WIPES
NDC: 67751-230 | Form: CLOTH
Manufacturer: Navajo Manufacturing Company Inc.
Category: otc | Type: HUMAN OTC DRUG LABEL
Date: 20250210

ACTIVE INGREDIENTS: BENZALKONIUM CHLORIDE 0.13 g/100 g
INACTIVE INGREDIENTS: CHLOROXYLENOL; WATER; ALOE BARBADENSIS LEAF JUICE; C12-15 ALCOHOLS

67751-230 CASEY'S ANTIBACTERIAL HAND WIPES

Active ingredient

Benzalkonium chloride 0.13%

Purpose

Antibacterial

Uses

to decrease bacteria on the skin

recommended for repeated use

Warnings

For exteral use only

When using this product keep away from eyes.

In case of eye contact, rinse eyes with water.

Stop use and ask a doctor if irritation or redness develop or lasts for more than 72 hours.

Keep out of reach of children.

If swallowed, get medical help or contact a Poison Control Center right away.

Directions

rub wipe thoroughly over all surfaces of both hands

allow to dry without wiping

supervise children under 6 years old

not recommended for infants

dispose of wipe in trash; do not flush

Inactive ingredients

Water, Fragrance, C12-15 Alcohols, Chloroxylenol, Aloe Barbadensis Leaf Juice

PACKAGE LABEL

15 COUNT
NDC: 67751-230-01